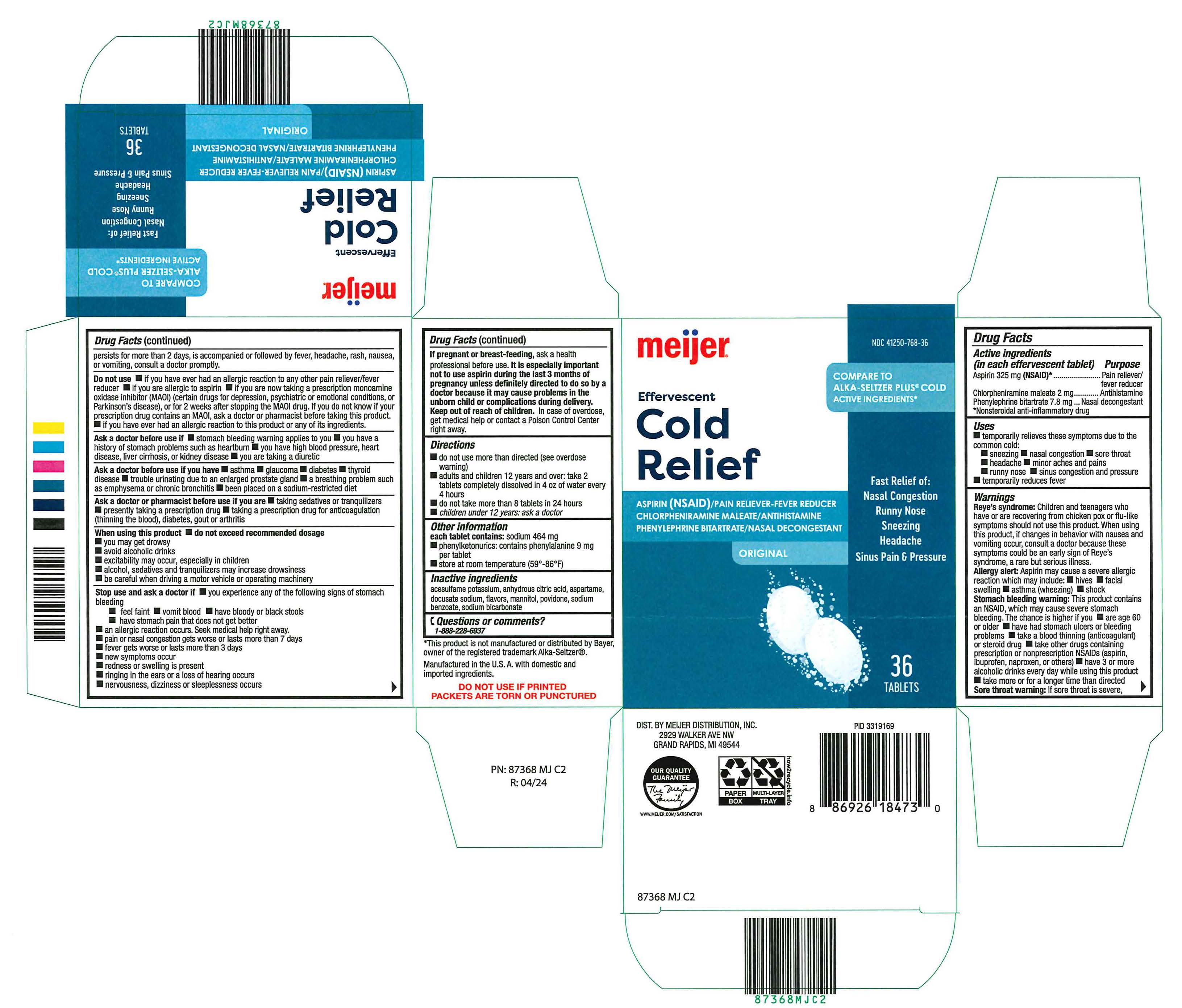 DRUG LABEL: Meijer Effervescent Cold Relief
NDC: 41250-768 | Form: TABLET, EFFERVESCENT
Manufacturer: Meijer Distribution Inc.
Category: otc | Type: HUMAN OTC DRUG LABEL
Date: 20241210

ACTIVE INGREDIENTS: ASPIRIN 325 mg/1 1; CHLORPHENIRAMINE MALEATE 2 mg/1 1; PHENYLEPHRINE BITARTRATE 7.8 mg/1 1
INACTIVE INGREDIENTS: ACESULFAME POTASSIUM; ASPARTAME; ANHYDROUS CITRIC ACID; DOCUSATE SODIUM; MANNITOL; POVIDONE; SODIUM BENZOATE; SODIUM BICARBONATE

Meijer Effervescent Cold Relief

Active ingredients

(in each effervescent tablet)

Aspirin 325 mg (NSAID)*

Chlorpheniramine maleate 2 mg

Phenylephrine bitartrate 7.8 mg

*Nonsteroidal anti-inflammatory drug

Purpose

Aspirin 325 mg (NSAID)*........................................Pain reliever/fever reducer

Chlorpheniramine maleate 2 mg............................Antihistamine

Phenylephrine bitartrate 7.8 mg.............................Nasal decongestant

*Nonsteroidal anti-inflammatory drug

Uses

■ temporarily relieves these symptoms due to the common cold:

■ sneezing ■ nasal congestion ■ sore throat ■ headache ■ minor aches and pains

■ runny nose ■ sinus congestion and pressure ■ temporarily reduces fever

Warnings

Reye’s syndrome: Children and teenagers who have or are recovering from chicken pox or flu-like symptoms should not use this product. When using this product, if changes in behavior with nausea and vomiting occur, consult a doctor because these symptoms could be an early sign of Reye’s syndrome, a rare but serious illness.

Allergy alert: Aspirin may cause a severe allergic reaction which may include: ■ hives ■ facial swelling ■ asthma (wheezing) ■ shock

Stomach bleeding warning: This product contains an NSAID, which may cause severe stomach bleeding. The chance is higher if you ■ are age 60 or older ■ have had stomach ulcers or bleeding problems ■ take a blood thinning (anticoagulant) or steroid drug ■ take other drugs containing prescription or nonprescription NSAIDs (aspirin, ibuprofen, naproxen, or others) ■ have 3 or more alcoholic drinks every day while using this product ■ take more or for a longer time than directed

Sore throat warning: If sore throat is severe, persists for more than 2 days, is accompanied or followed by fever, headache, rash, nausea, or vomiting, consult a doctor promptly.

Do not use ■ if you have ever had an allergic reaction to any other pain reliever/fever reducer ■ if you are allergic to aspirin ■ if you are now taking a prescription monoamine oxidase inhibitor (MAOI) (certain drugs for depression, psychiatric or emotional conditions, or Parkinson’s disease), or for 2 weeks after stopping the MAOI drug. If you do not know if your prescription drug contains an MAOI, ask a doctor or pharmacist before taking this product. ■ if you have ever had an allergic reaction to this product or any of its ingredients.

Ask a doctor before use if ■ stomach bleeding warning applies to you ■ you have a history of stomach problems such as heartburn ■ you have high blood pressure, heart disease, liver cirrhosis, or kidney disease ■ you are taking a diuretic

Ask a doctor before use if you have ■ asthma ■ glaucoma ■ diabetes ■ thyroid disease ■ trouble urinating due to an enlarged prostate gland ■ a breathing problem such as emphysema or chronic bronchitis ■ been placed on a sodium-restricted diet

Ask a doctor or pharmacist before use if you are ■ taking sedatives or tranquilizers ■ presently taking a prescription drug ■ taking a prescription drug for anticoagulation (thinning the blood), diabetes, gout or arthritis

When using this product ■ do not exceed recommended dosage

■ you may get drowsy

■ avoid alcoholic drinks

■ excitability may occur, especially in children

■ alcohol, sedatives and tranquilizers may increase drowsiness

■ be careful when driving a motor vehicle or operating machinery

Stop use and ask a doctor if ■ you experience any of the following signs of stomach bleeding

■ feel faint ■ vomit blood ■ have bloody or black stools ■ have stomach pain that does not get better

■ an allergic reaction occurs. Seek medical help right away.

■ pain or nasal congestion gets worse or lasts more than 7 days

■ fever gets worse or lasts more than 3 days

■ new symptoms occur

■ redness or swelling is present

■ ringing in the ears or a loss of hearing occurs

■ nervousness, dizziness or sleeplessness occurs

If pregnant or breast-feeding, ask a health professional before use. It is especially important not to use aspirin during the last 3 months of pregnancy unless definitely directed to do so by a doctor because it may cause problems in the unborn child or complications during delivery.

Keep out of reach of children

In case of overdose, get medical help or contact a Poison Control Center right away.

Directions

■ do not use more than directed (see overdose warning)

■ adults and children 12 years and over: take 2 tablets completely dissolved in 4 oz of water every 4 hours

■ do not take more than 8 tablets in 24 hours

■ children under 12 years: ask a doctor

Other information

each tablet contains: sodium 464 mg

■ phenylketonurics: contains phenylalanine 9 mg per tablet

■ store at room temperature (59°-86°F)

Inactive ingredients

acesulfame potassium, anhydrous citric acid, aspartame, docusate sodium, flavors, mannitol, povidone, sodium

benzoate, sodium bicarbonate

Questions or comments?

1-888-228-6937